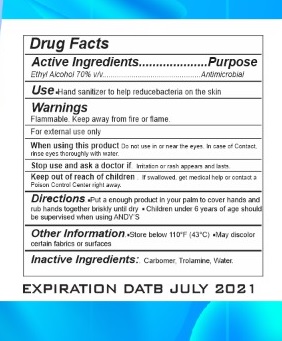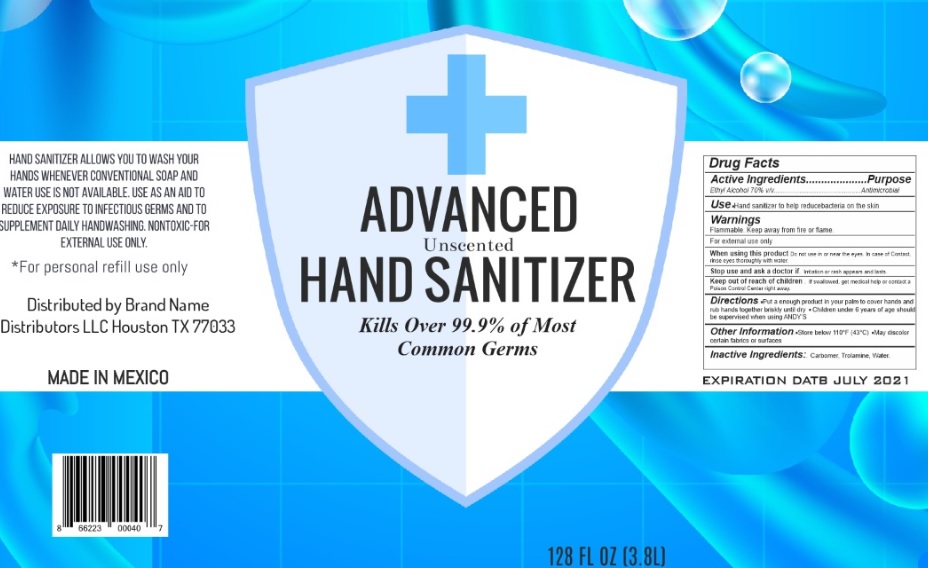 DRUG LABEL: Plus Advanced
NDC: 73755-300 | Form: GEL
Manufacturer: Brand Name Distributor LLC
Category: otc | Type: HUMAN OTC DRUG LABEL
Date: 20200702

ACTIVE INGREDIENTS: ALCOHOL 0.7 mL/1 mL
INACTIVE INGREDIENTS: CARBOMER HOMOPOLYMER, UNSPECIFIED TYPE 0.0025 mL/1 mL; TROLAMINE 0.125 mL/1 mL; WATER 0.289 mL/1 mL

Active Ingredient(s)

Ethyl Alcohol 70% v/v...............................................Antimicrobial

Purpose

Antimicrobial, Hand Sanitizer

Use

Hand Sanitizer to help reduce bacteria that potentially can cause disease. For use when soap and water are not available.

Warnings

Flammable. Keep away from heat or flame

Do not use

- in children less than 2 months of age
- For external use only

When using this product keep out of eyes, ears, and mouth. In case of contact with eyes, rinse eyes thoroughly with water.
Stop use and ask a doctor if irritation or rash occurs. These may be signs of a serious condition.
Keep out of reach of children. If swallowed, get medical help or contact a Poison Control Center right away.

Stop use and ask a doctor if irritation or rash occurs. These may be signs of a serious condition.

Keep out of reach of children. If swallowed, get medical help or contact a Poison Control Center right away.

Directions

Put a enough product in your palm to cover hands and rub hands together briskly until dry Children under 6 years of age should be supervised when using

Other information

Store below 110°F (43°C) May discolor certain fabrics or surfaces

Inactive ingredients

Inactive Ingredients:. Carbomer, Trolamine, Water

Package Label - Principal Display Panel

+ Advanced Unscented Hand Sanitizer

KILLS OVER 99.9 OF MOST COMMON GERMS

128 FL OZ (3.8L)